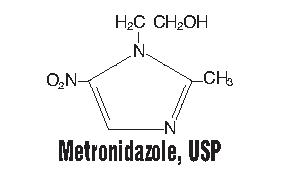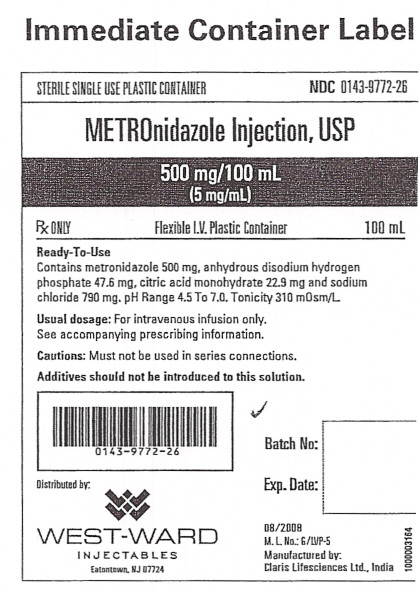 DRUG LABEL: Metronidazole
NDC: 0143-9772 | Form: INJECTION, SOLUTION
Manufacturer: West-ward Pharmaceutical Corp
Category: prescription | Type: HUMAN PRESCRIPTION DRUG LABEL
Date: 20100202

ACTIVE INGREDIENTS: METRONIDAZOLE 500 mg/100 mL
INACTIVE INGREDIENTS: SODIUM CHLORIDE 790 ug/100 mL; SODIUM PHOSPHATE, DIBASIC 47.6 mg/100 mL; ANHYDROUS CITRIC ACID 22.9 mg/100 mL; WATER

Metronidazole Injection

To reduce the development of drug-resistant bacteria and maintain the effectiveness of Metronidazole Injection, USP and other antibacterial drugs, Metronidazole Injection, USP should be used only to treat or prevent infections that are proven or strongly suspected to be caused by bacteria.

WARNING

Metronidazole has been shown to be carcinogenic in mice and rats (see Precautions). Its use, therefore, should be reserved for the conditions described in the Indications and Usage section below.

DESCRIPTION

Metronidazole Injection, USP, is a parenteral dosage form of the synthetic antibacterial agent 1-(ß-hydroxyethyl)-2-methyl-5- nitroimidazole.

Metronidazole Injection, USP, in 100 mL single dose plastic container, is a sterile, nonpyrogenic, iso-osmotic, buffered solution of 500 mg Metronidazole, USP, 790 mg Sodium Chloride, USP, 47.6 mg Anhydrous Disodium Hydrogen Phosphate, USP and 22.9 mg Citric Acid Monohydrate, USP. Metronidazole Injection, USP has an osmolarity of 310 mOsmol/L (calc) and a pH of 5.5 (4.5 to 7.0). Each container contains 14 mEq of sodium. The plastic container is fabricated from a specially formulated polyvinyl chloride plastic. Water can permeate from inside the container into the overwrap in amounts insufficient to affect the solution significantly. Solutions in contact with the plastic container can leach out certain of its chemical components in very small amounts within the expiration period, e.g., di-2-ethylhexyl phthalate (DEHP), up to 5 parts per million. However, the safety of the plastic has been confirmed in tests in animals according to USP biological tests for plastic containers.

CLINICAL PHARMACOLOGY

Metronidazole is a synthetic antibacterial compound. Disposition of metronidazole in the body is similar for both oral and intravenous dosage forms, with an average elimination half-life in healthy humans of eight hours.

The major route of elimination of metronidazole and its metabolites is via the urine (60-80% of the dose), with fecal excretion accounting for 6-15% of the dose. The metabolites that appear in the urine result primarily from side-chain oxidation [1-(ß-hydroxyethyl)-2-hydroxymethyl-5-nitroimidazole and 2-methyl-5-nitroimidazole-1-yl-acetic acid] and glucuronide conjugation, with unchanged metronidazole accounting for approximately 20% of the total. Renal clearance of metronidazole is approximately 10 mL/min/1.73 m^2.

Metronidazole is the major component appearing in the plasma, with lesser quantities of the 2-hydroxymethyl metabolite also being present. Less than 20% of the circulating metronidazole is bound to plasma proteins. Both the parent compound and the metabolite possess in vitro bactericidal activity against most strains of anaerobic bacteria.

Metronidazole appears in cerebrospinal fluid, saliva and breast milk in concentrations similar to those found in plasma. Bactericidal concentrations of metronidazole have also been detected in pus from hepatic abscesses.

Plasma concentrations of metronidazole are proportional to the administered dose. An eight-hour intravenous infusion of 100-4,000 mg of metronidazole in normal subjects showed a linear relationship between dose and peak plasma concentration.

In patients treated with intravenous metronidazole, using a dosage regimen of 15 mg/kg loading dose followed six hours later by 7.5 mg/kg every six hours; peak steady-state plasma concentrations of metronidazole averaged 25 mcg/mL with trough (minimum) concentrations averaging 18 mcg/mL.

Decreased renal function does not alter the single-dose pharmacokinetics of metronidazole. However, plasma clearance of metronidazole is decreased in patients with decreased liver function.

In one study newborn infants appeared to demonstrate diminished capacity to eliminate metronidazole. The elimination half-life, measured during the first three days of life, was inversely related to gestational age. In infants whose gestational ages were between 28 and 40 weeks, the corresponding elimination half-lives ranged from 109 to 22.5 hours.

Microbiology:

Metronidazole is active in vitro against most obligate anaerobes, but does not appear to possess any clinically relevant activity against facultative anaerobes or obligate aerobes. Against susceptible organisms, metronidazole is generally bactericidal at concentrations equal to or slightly higher than the minimal inhibitory concentrations. Metronidazole has been shown to have in vitro and clinical activity against the following organisms:

Anaerobic gram-negative bacilli, including:
Bacteroides species, including the Bacteroides fragilis group (B. fragilis, B. distasonis, B. ovatus, B. thetaiotaomicron, B. vulgatus)
Fusobacterium species

Anaerobic gram-positive bacilli, including:
Clostridium species and susceptible strains of Eubacterium

Anaerobic gram-positive cocci, including:
Peptococcus species
Peptostreptococcus species

Susceptibility Tests:

Bacteriologic studies should be performed to determine the causative organisms and their susceptibility to metronidazole; however, the rapid, routine susceptibility testing of individual isolates of anaerobic bacteria is not always practical, and therapy may be started while awaiting these results.

Quantitative methods give the most accurate estimates of susceptibility to antibacterial drugs. A standardized agar dilution method and a broth microdilution method are recommended^1.

Control strains are recommended for standardized susceptibility testing. Each time the test is performed, one or more of the following strains should be included: Eubacterium lentum ATCC 43055, Bacteroides fragilis ATCC 25285, and Bacteroides thetaiotaomicron ATCC 29741. The mode metronidazole MICs for those three strains are reported to be 0.125, 0.25, and 0.5 mcg/mL, respectively.

A clinical laboratory test is considered under acceptable control if the results of the control strains are within one doubling dilution of the mode MICs reported for metronidazole.

A bacterial isolate may be considered susceptible if the MIC value for metronidazole is not more than 16 mcg/mL. An organism is considered resistant if the MIC is greater than 16 mcg/mL. A report of "resistant" from the laboratory indicates that the infecting organism is not likely to respond to therapy.

INDICATIONS AND USAGE

Treatment of Anaerobic Infections

Metronidazole Injection, USP is indicated in the treatment of serious infections caused by susceptible anaerobic bacteria. Indicated surgical procedures should be performed in conjunction with Metronidazole Injection, USP therapy. In a mixed aerobic and anaerobic infection, antibiotics appropriate for the treatment of the aerobic infection should be used in addition to Metronidazole Injection, USP.

Metronidazole Injection, USP is effective in Bacteroides fragilis infections resistant to clindamycin, chloramphenicol and penicillin.

Intra-Abdominal Infections, including peritonitis, intra-abdominal abscess and liver abscess, caused by Bacteroides species including the B. fragilis group (B. fragilis, B. distasonis, B. ovatus, B. thetaiotaomicron, B. vulgatus), Clostridium species, Eubacterium species, Peptococcus species and Peptostreptococcus species.

Skin and Skin Structure Infections caused by Bacteroides species including the B. fragilis group, Clostridium species, Peptococcus species, Peptostreptococcus species and Fusobacterium species.

Gynecologic Infections, including endometritis, endomyometritis, tubo-ovarian abscess and postsurgical vaginal cuff infection, caused by Bacteroides species including the B. fragilis group, Clostridium species, Peptostreptococcus species and Fusobacterium species.

Bacterial Septicemia caused by Bacteroides species including the B. fragilis group and Clostridium species.

Bone and Joint Infections, as adjunctive therapy, caused by Bacteroides species including the B. fragilis group.

Central Nervous System (CNS) Infections, including meningitis and brain abscess, caused by Bacteroides species including the B. fragilis group.

Lower Respiratory Tract Infections, including pneumonia, empyema and lung abscess, caused by Bacteroides species including the B. fragilis group.

Endocarditis caused by Bacteroides species including the B. fragilis group.

Prophylaxis

The prophylactic administration of Metronidazole Injection, USP preoperatively, intraoperatively and postoperatively may reduce the incidence of postoperative infection in patients undergoing elective colorectal surgery, which is classified as contaminated or potentially contaminated.

Prophylactic use of Metronidazole Injection, USP should be discontinued within 12 hours after surgery. If there are signs of infection, specimens for cultures should be obtained for the identification of the causative organism(s) so that appropriate therapy may be given (see Dosage and Administration).

To reduce the development of drug-resistant bacteria and maintain the effectiveness of Metronidazole Injection, USP and other antibacterial drugs, Metronidazole Injection, USP should be used only to treat or prevent infections that are proven or strongly suspected to be caused by susceptible bacteria. When culture and susceptibility information are available, they should be considered in selecting or modifying antibacterial therapy. In the absence of such data, local epidemiology and susceptibility patterns may contribute to the empiric selection of therapy.

CONTRAINDICATIONS

Metronidazole Injection, USP is contraindicated in patients with a prior history of hypersensitivity to metronidazole or other nitroimidazole derivatives.

WARNINGS

Central and Peripheral Nervous System Effects:

Convulsive seizures, encephalopathy, aseptic meningitis, optic and peripheral neuropathy, the latter characterized mainly by numbness or paresthesia of an extremity, have been reported in patients treated with metronidazole. The appearance of abnormal neurologic signs demands the prompt evaluation of the benefit/risk ratio of the continuation of therapy.

PRECAUTIONS

General

Patients with severe hepatic disease metabolize metronidazole slowly, with resultant accumulation of metronidazole and its metabolites in the plasma. Accordingly, for such patients, doses below those usually recommended should be administered cautiously.

Administration of solutions containing sodium ions may result in sodium retention. Care should be taken when administering Metronidazole Injection, USP to patients receiving corticosteroids or to patients predisposed to edema.

Known or previously unrecognized candidiasis may present more prominent symptoms during therapy with Metronidazole Injection, USP and requires treatment with a candidacidal agent.

Prescribing Metronidazole Injection, USP in the absence of a proven or strongly suspected bacterial infection or a prophylactic indication is unlikely to provide benefit to the patient and increases the risk of the development of drug-resistant bacteria.

Laboratory Tests

Metronidazole is a nitroimidazole, and should be used with care in patients with evidence of or history of blood dyscrasia. A mild leukopenia has been observed during its administration; however, no persistent hemotologic abnormalities attributable to metronidazole have been observed in clinical studies. Total and differential leukocyte counts are recommended before and after therapy.

Drug Interactions

Metronidazole has been reported to potentiate the anticoagulant effect of warfarin and other oral coumarin anticoagulants, resulting in a prolongation of prothrombin time. This possible drug interaction should be considered when Metronidazole Injection, USP is prescribed for patients on this type of anticoagulant therapy.

The simultaneous administration of drugs that induce microsomal liver enzyme activity, such as phenytoin or phenobarbital, may accelerate the elimination of metronidazole, resulting in reduced plasma levels; impaired clearance of phenytoin has also been reported.

The simultaneous administration of drugs that decrease microsomal liver enzyme activity, such as cimetidine, may prolong the half-life and decrease plasma clearance of metronidazole.

Alcoholic beverages should not be consumed during metronidazole therapy because abdominal cramps, nausea, vomiting, headaches and flushing may occur.

Psychotic reactions have been reported in alcoholic patients who are using metronidazole and disulfiram concurrently. Metronidazole should not be given to patients who have taken disulfiram within the last two weeks.

Drug/Laboratory Test Interactions

Metronidazole may interfere with certain types of determinations of serum chemistry values, such as aspartate aminotransferase (AST, SGOT), alanine aminotransferase (ALT, SGPT), lactate dehydrogenase (LDH), triglycerides and hexokinase glucose. Values of zero may be observed. All of the assays in which interference has been reported involve enzymatic coupling of the assay to oxidation-reduction of nicotine adenine dinucleotide (NAD ^+ = NADH). Interference is due to the similarity in absorbance peaks of NADH (340nm) and metronidazole (322nm) at pH7.

Carcinogenesis, Mutagenesis, Impairment of Fertility

Tumorigenicity in Rodents - Metronidazole has shown evidence of carcinogenic activity in studies involving chronic, oral administration in mice and rats, but similar studies in the hamster gave negative results. Also, metronidazole has shown mutagenic activity in a number of in vitro assay systems, but studies in mammals (in vivo) failed to demonstrate a potential for genetic damage.

Pregnancy: Teratogenic Effects

Pregnancy Category B. Metronidazole crosses the placental barrier and enters the fetal circulation rapidly. Reproduction studies have been performed in rats at doses up to five times the human dose and have revealed no evidence of impaired fertility or harm to the fetus due to metronidazole. Metronidazole administered intraperitoneally to pregnant mice at approximately the human dose caused fetotoxicity; administered orally to pregnant mice, no fetotoxicity was observed. There are, however, no adequate and well-controlled studies in pregnant women. Because animal reproduction studies are not always predictive of human response, and because metronidazole is a carcinogen in rodents, these drugs should be used during pregnancy only if clearly needed.

Nursing Mothers

Because of the potential for tumorigenicity shown for metronidazole in mouse and rat studies, a decision should be made whether to discontinue nursing or to discontinue the drug, taking into account the importance of the drug to the mother. Metronidazole is secreted in breast milk in concentrations similar to those found in plasma.

Pediatric Use

Safety and effectiveness in pediatric patients have not been established.

INFORMATION FOR PATIENTS

Patients should be counseled that antibacterial drugs including Metronidazole Injection, USP should only be used to treat bacterial infections. They do not treat viral infections (e.g., the common cold). When Metronidazole Injection, USP is prescribed to treat a bacterial infection, patients should be told that although it is common to feel better early in the course of therapy, the medication should be taken exactly as directed. Skipping doses or not completing the full course of therapy may (1) decrease the effectiveness of the immediate treatment and (2) increase the likelihood that bacteria will develop resistance and will not be treatable by Metronidazole Injection, USP or other antibacterial drugs in the future.

ADVERSE REACTIONS

The most serious adverse reactions reported in patients treated with metronidazole injection have been convulsive seizures, encephalopathy, aseptic meningitis, optic and peripheral neuropathy, the latter characterized mainly by numbness or paresthesia of an extremity. Since persistent peripheral neuropathy has been reported in some patients receiving prolonged oral administration of metronidazole, patients should be observed carefully if neurologic symptoms occur and a prompt evaluation made of the benefit/risk ratio of the continuation of therapy.

The following reactions have also been reported during treatment with Metronidazole Injection, USP.

Gastrointestinal: Nausea, vomiting, abdominal discomfort, diarrhea and an unpleasant metallic taste.

Hematopoietic: Reversible neutropenia (leukopenia).

Dermatologic: Erythematous rash and pruritus.

Central Nervous System: Encephalopathy, aseptic meningitis, convulsive seizures, optic neuropathy, peripheral neuropathy, dizziness, vertigo, incoordination, ataxia, confusion, dysarthria, irritability, depression, weakness, and insomnia.

Local Reactions: Thrombophlebitis after intravenous infusion. This reaction can be minimized or avoided by avoiding prolonged use of indwelling intravenous catheters.

Other: Fever. Instances of darkened urine have also been reported, and this manifestation has been the subject of a special investigation. Although the pigment, which is probably responsible for this phenomenon, has not been positively identified, it is almost certainly a metabolite of metronidazole and seems to have no clinical significance.

The following adverse reactions have been reported during treatment with oral metronidazole:

Gastrointestinal: Nausea, sometimes accompanied by headache, anorexia and occasionally vomiting; diarrhea, epigastric distress, abdominal cramping and constipation.

Mouth: A sharp, unpleasant metallic taste is not unusual. Furry tongue, glossitis and stomatitis have occurred; these may be associated with a sudden overgrowth of Candida, which may occur during effective therapy.

Hematopoietic: Reversible neutropenia (leukopenia); rarely, reversible thrombocytopenia.

Cardiovascular: Flattening of the T-wave may be seen in electrocardiographic tracings.

Central Nervous System: Convulsive seizures, peripheral neuropathy, dizziness, vertigo, incoordination, ataxia, confusion, irritability, depression, weakness, and insomnia.

Hypersensitivity: Urticaria, erythematous rash, Stevens-Johnson Syndrome, flushing, nasal congestion, dryness of the mouth (or vagina or vulva) and fever.

Renal: Dysuria, cystitis, polyuria, incontinence, a sense of pelvic pressure and darkened urine.

Other: Proliferation of Candida in the vagina, dyspareunia, decrease of libido, proctitis and fleeting joint pains sometimes resembling “serum sickness.” If patients receiving metronidazole drink alcoholic beverages, they may experience abdominal distress, nausea, vomiting, flushing or headache. A modification of the taste of alcoholic beverages has also been reported. Rare cases of pancreatitis, which abated on withdrawal of the drug, have been reported.

Crohn's disease patients are known to have an increased incidence of gastrointestinal and certain extraintestinal cancers. There have been some reports in the medical literature of breast and colon cancer in Crohn's disease patients who have been treated with metronidazole at high doses for extended periods of time. A cause and effect relationship has not been established. Crohn's disease is not an approved indication for Metronidazole Injection, USP.

OVERDOSAGE

Use of dosages of intravenous metronidazole higher than those recommended has been reported. These include the use of 27 mg/kg three times a day for 20 days, and the use of 75 mg/kg as a single loading dose followed by 7.5 mg/kg maintenance doses. No adverse reactions were reported in either of the two cases.

Single oral dose of metronidazole, up to 15 g, have been reported in suicide attempts and accidental overdoses. Symptoms reported included nausea, vomiting and ataxia.

Oral metronidazole has been studied as a radiation sensitizer in the treatment of malignant tumors. Neurotoxic effects, including seizures and peripheral neuropathy, have been reported after 5 to 7 days of doses of 6 to 10.4 g every other day.

Treatment: There is no specific antidote for overdose; therefore, management of the patient should consist of symptomatic and supportive therapy.

DOSAGE AND ADMINISTRATION

In elderly patients the pharmacokinetics of metronidazole may be altered and therefore monitoring of serum levels may be necessary to adjust the metronidazole dosage accordingly.

Treatment of Anaerobic Infections

The recommended dosage schedule for adults is:

Loading Dose: 15 mg/kg infused over one hour (approximately 1 g for a 70-kg adult).
Maintenance Dose: 7.5 mg/kg infused over one hour every six hours (approximately 500 mg for a 70-kg adult).
The first maintenance dose should be instituted six hours following the initiation of the loading dose.

Parenteral therapy may be changed to oral metronidazole when conditions warrant, based upon the severity of the disease and the response of the patient to Metronidazole Injection, USP treatment. The usual adult oral dosage is 7.5 mg/kg every six hours.

A maximum of 4 g should not be exceeded during a 24 hour period.

Patients with severe hepatic disease metabolize metronidazole slowly, with resultant accumulation of metronidazole and its metabolites in the plasma. Accordingly, for such patients, doses below those usually recommended should be administered cautiously. Close monitoring of plasma metronidazole levels^2 and toxicity is recommended.

In patients receiving Metronidazole Injection, USP in whom gastric secretions are continuously removed by nasogastric aspiration, sufficient metronidazole may be removed in the aspirate to cause a reduction in serum levels.

The dose of Metronidazole Injection, USP should not be specifically reduced in anuric patients since accumulated metabolites may be rapidly removed by dialysis.

The usual duration of therapy is 7 to 10 days; however, infections of the bone and joint, lower respiratory tract and endocardium may require longer treatment.

Prophylaxis

For surgical prophylactic use, to prevent postoperative infection in contaminated or potentially contaminated colorectal surgery, the recommended dosage schedule for adults is:

1. 15 mg/kg infused over 30 to 60 minutes and completed approximately one hour before surgery; followed by
2. 7.5 mg/kg infused over 30 to 60 minutes at 6 and 12 hours after the initial dose.

It is important that (1) administration of the initial preoperative dose be completed approximately one hour before surgery so that adequate drug levels are present in the serum and tissues at the time of initial incision, and (2) Metronidazole Injection, USP be administered, if necessary, at 6-hour intervals to maintain effective drug levels. Prophylactic use of Metronidazole Injection, USP should be limited to the day of surgery only, following the above guidelines.

Caution: Metronidazole Injection, USP is to be administered by slow intravenous drip infusion only, either as a continuous or intermittent infusion. Additives should not be introduced into Metronidazole Injection, USP. If used with a primary intravenous fluid system, the primary solution should be discontinued during metronidazole infusion. DO NOT USE EQUIPMENT CONTAINING ALUMINUM (e.g., NEEDLES, CANNULAE) THAT WOULD COME IN CONTACT WITH THE DRUG SOLUTION.

Parenteral drug products should be inspected visually for particulate matter and discoloration prior to administration, whenever solution and container permit.

HOW SUPPLIED

Metronidazole Injection, USP is sterile and is supplied in 100 mL single dose plastic containers, each containing an iso-osmotic, buffered solution of 500 mg metronidazole as follows:

NDC 0143-9772-26500 mg/100 mL

Two groups of 12 bags each are placed in a carton, separated by a divider. Four cartons are then packed into a shipper. Store at 20°-25°C (68°-77°F) (see USP controlled room temperature). Protect from light during storage. Avoid excessive heat. Protect from freezing. Do not remove unit from overwrap until ready for use. The overwrap is a moisture barrier. The inner bag maintains the sterility of the product. After removing overwrap, check for minute leaks by squeezing the inner bag firmly. If leaks are found, discard solution as sterility may be impaired.

Directions for Use of Plastic Container

Metronidazole Injection, USP is a ready-to-use iso-osmotic solution. No dilution or buffering is required. Do not refrigerate. Each container of Metronidazole Injection, USP contains 14 mEq of sodium.

Warning: Do not use plastic containers in series connections. Such use could result in air embolism due to residual air being drawn from the primary container before administration of the fluid from the secondary container is completed.

To open
Tear overwrap at the top and remove solution container. Some opacity of the plastic due to moisture absorption during the sterilization process may be observed. This is normal and does not affect the solution quality or safety. The opacity will diminish gradually. Check for leaks. Do not add supplementary medication.

Preparation for Administration

1. Suspend container from eyelet support.
2. Remove plastic protector from outlet port at bottom of container.
3. Attach administration set. Refer to complete directions accompanying set.

REFERENCES

1. M11-A5-Methods for Antimicrobial Susceptibility Testing of Anaerobic Bacteria; approved Standard-Fifth Edition, National Committee for Clinical Laboratory Standards; and Sutter, et al.: Collaborative Evaluation of a Proposed Reference Dilution Method of Susceptibility Testing of Anaerobic Bacteria, Antimicrob. Agents Chemother. 16:495-502 (Oct.) 1979; and Tally, et al.: In Vitro Activity of Thienamycin, Antimicrob. Agents Chemother. 14:436-438 (Sept.) 1978.
2. Ralph, E.D. and Kirby, W.M.M.: Bioassay of Metronidazole with Either Anaerobic and Aerobic Incubation, J. Infect. Dis. 132:587-591 (Nov.) 1975; or Gulaid, et al.: Determination of Metronidazole and its Major Metabolites in Biological Fluids by High Pressure Liquid Chromatography. BR. J. Clin. Pharmacol. 6:430-432, 1978.

Manufactured by:
Claris Lifesciences Ltd. India

Distributed by:
West-ward Injectables
Eatontown, NJ 07724

PRINCIPAL DISPLAY PANEL

Metronidazole Injection, USP 500 mg/100 mL (5 mg/mL)